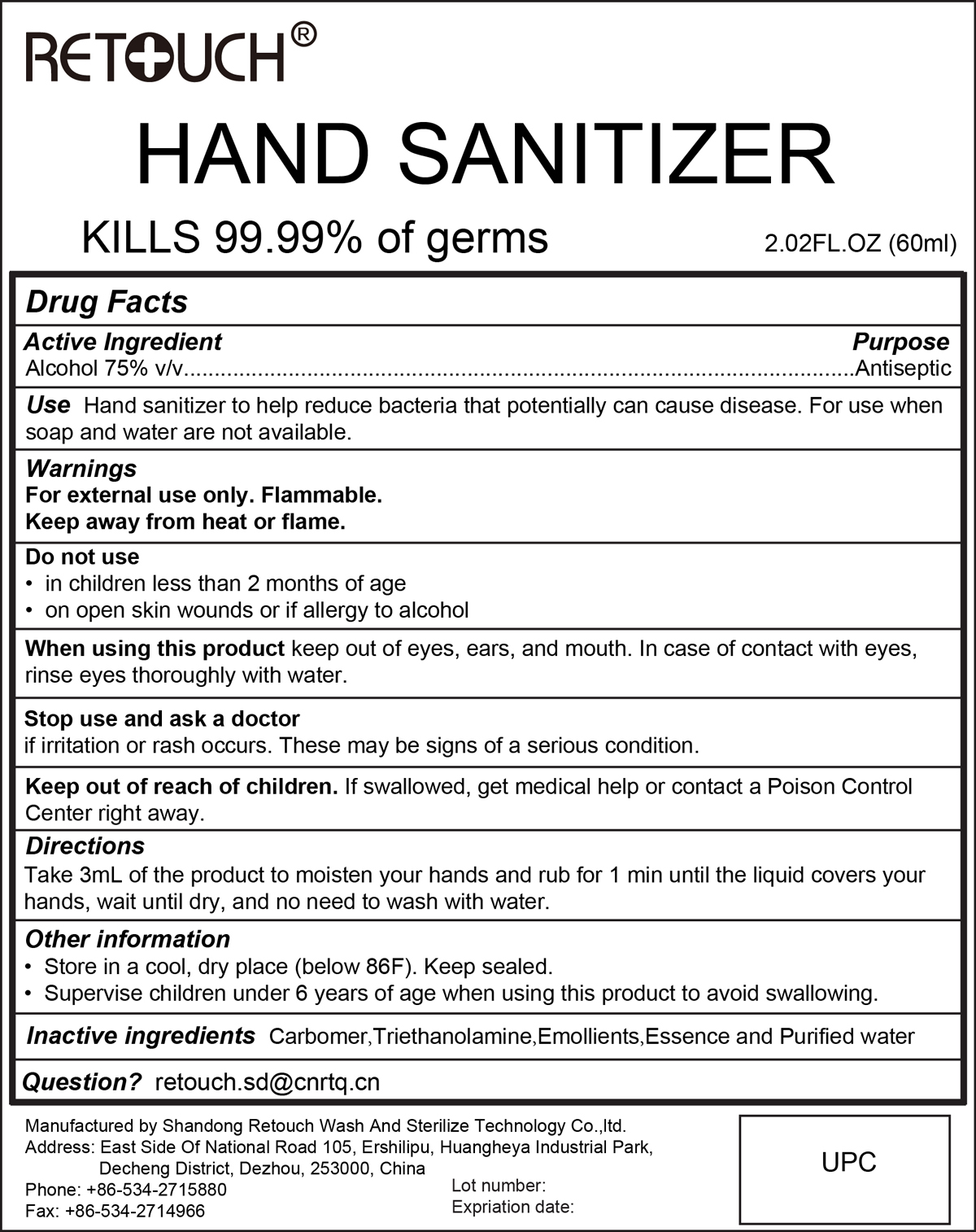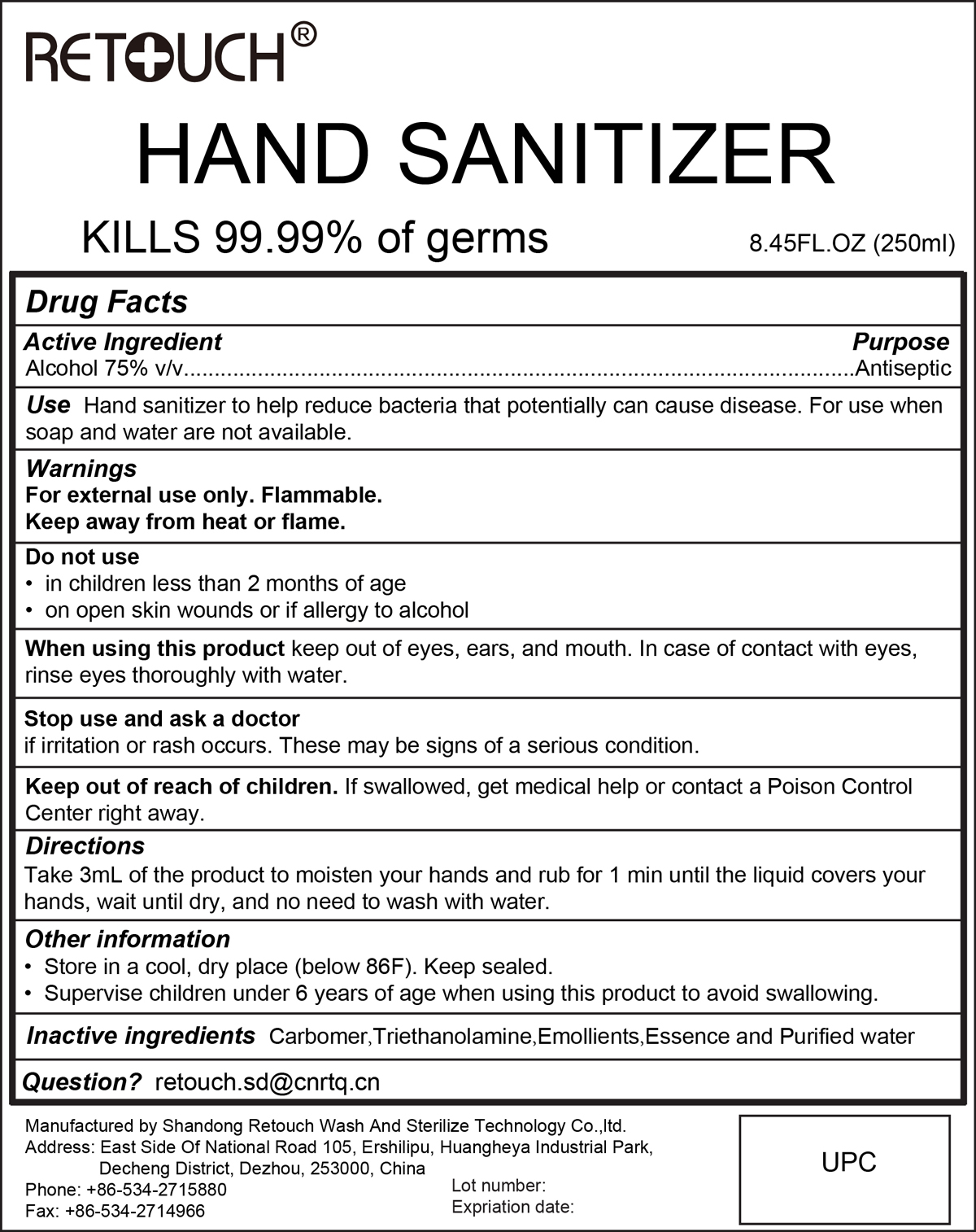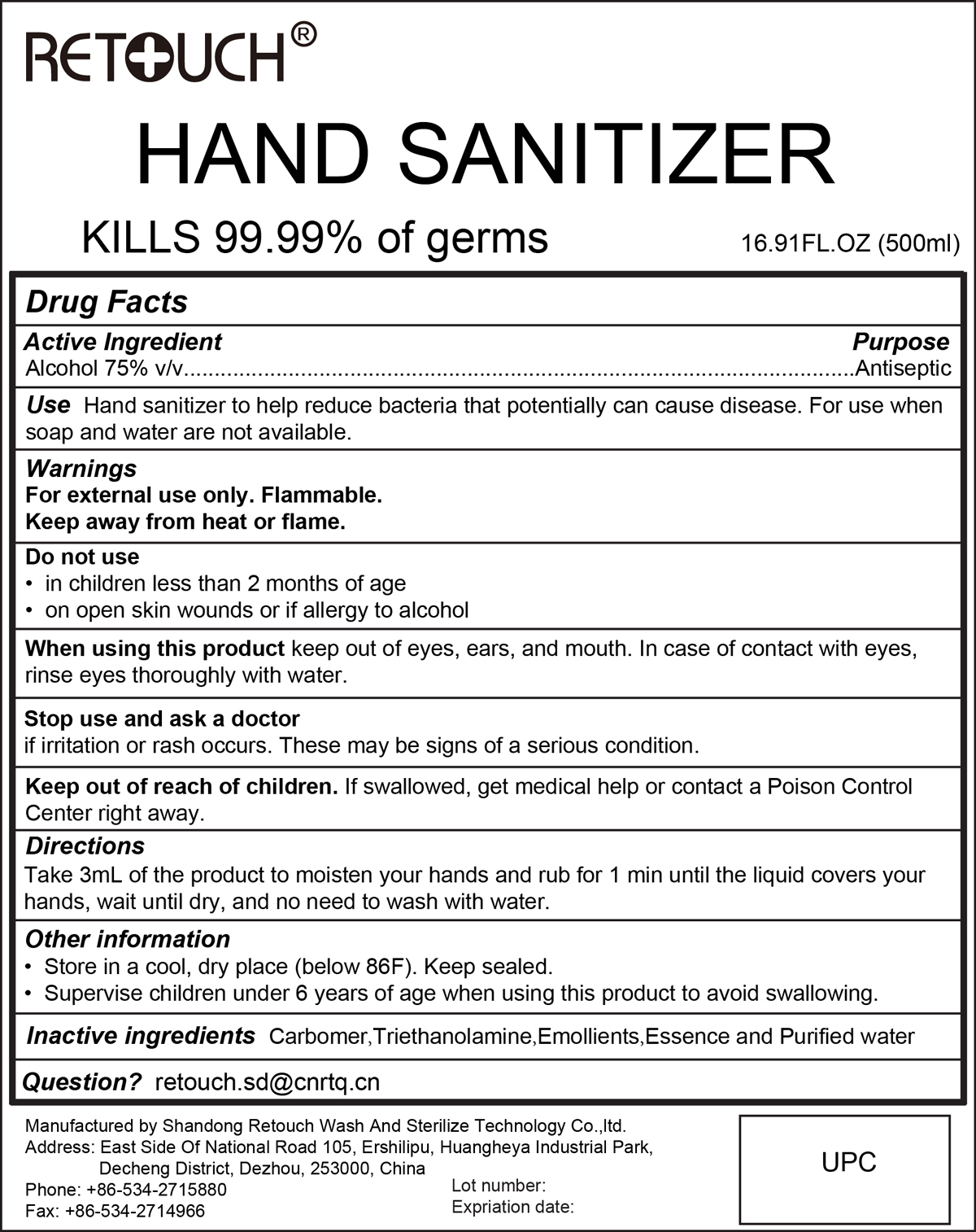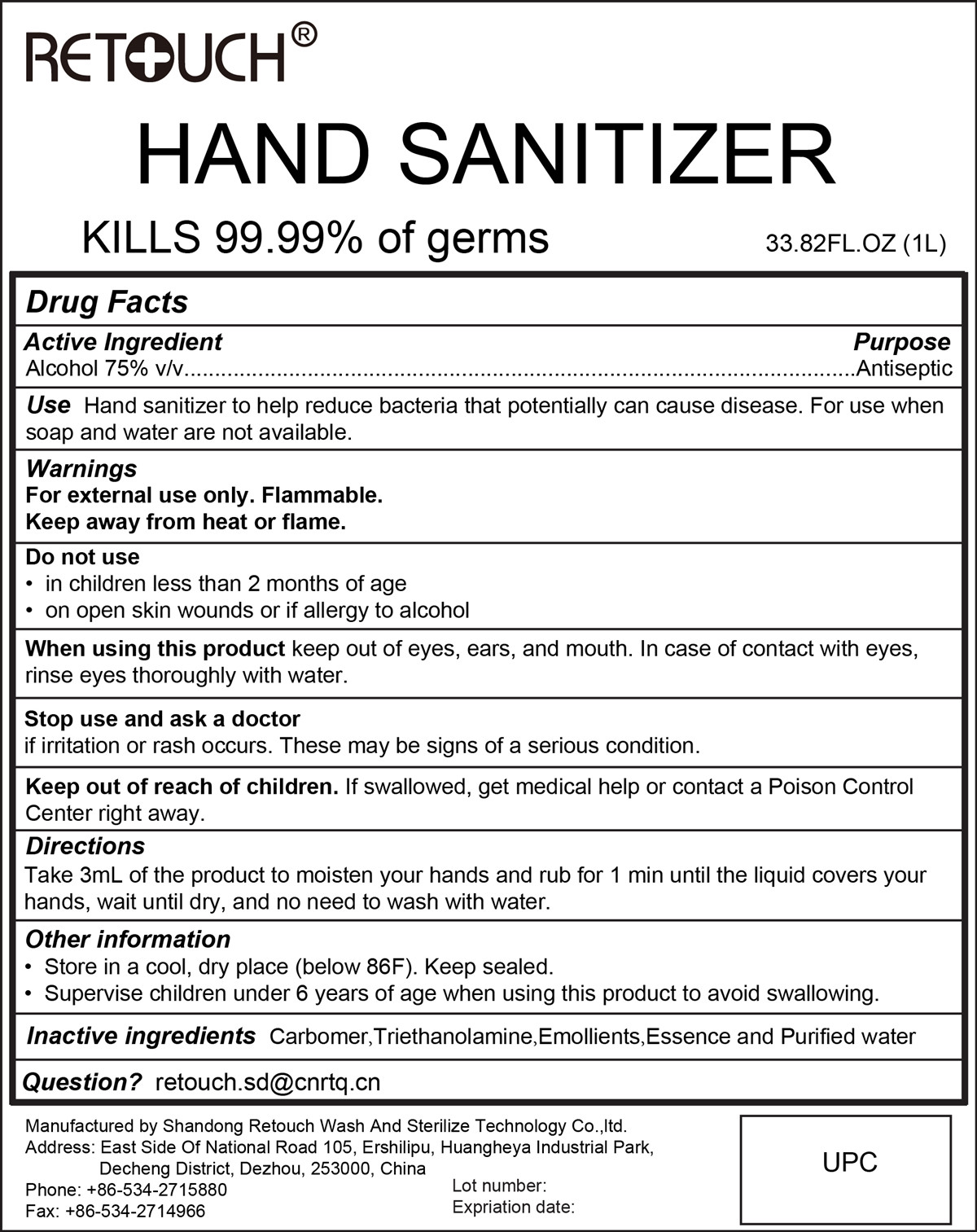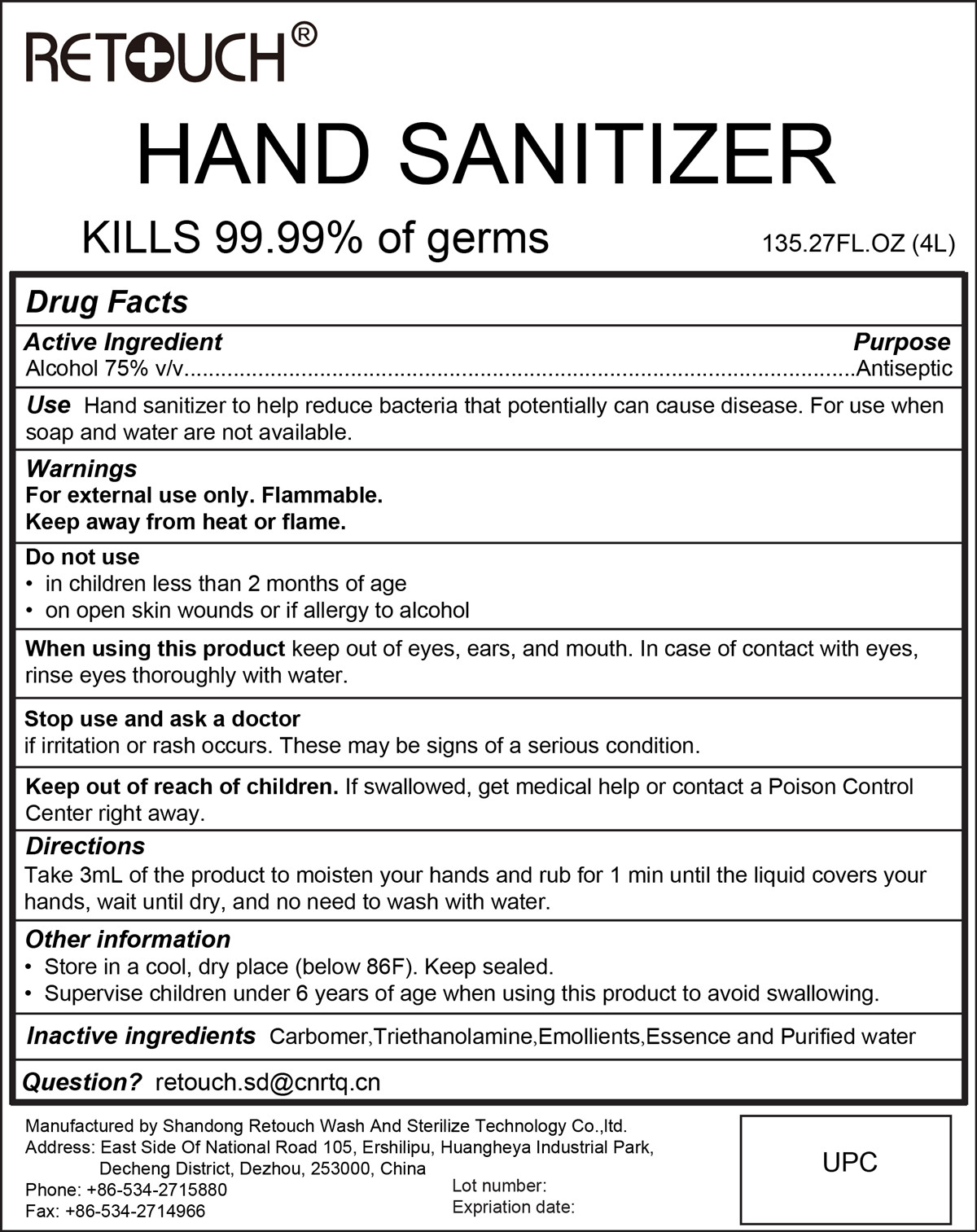 DRUG LABEL: 75% Hand Sanitizer
NDC: 75532-001 | Form: GEL
Manufacturer: Shandong Retouch Wash And Sterilize Technology Co.,ltd.
Category: otc | Type: HUMAN OTC DRUG LABEL
Date: 20230210

ACTIVE INGREDIENTS: ALCOHOL 75 mL/100 mL
INACTIVE INGREDIENTS: CARBOMER 940; TROLAMINE; WATER

75% Hand Sanitizer

Active Ingredient(s)

Alcohol 75% v/v. Purpose: Antiseptic

Purpose

Antiseptic, Hand Sanitizer

Use

Hand Sanitizer to help reduce bacteria that potentially can cause disease. For use when soap and water are not available.

Warnings

For external use only. Flammable.

Keep away from heat or flame

Do not use

- in children less than 2 months of age
- on open skin wounds or if allergy to alcohol

When using this product keep out of eyes, ears, and mouth. In case of contact with eyes, rinse eyes thoroughly with water.

Stop use and ask a doctor if irritation or rash occurs. These may be signs of a serious condition.

Keep out of reach of children. If swallowed, get medical help or contact a Poison Control Center right away.

Directions

Take 3mL of the product to moisten your hands and rub for 1 min until the liquid covers your hands, wait until dry, and no need to wash with water.

Other information

Store in a cool, dry place (below 86F). Keep sealed.

Supervise children under 6 years of age when using this product to avoid swallowing.

Inactive ingredients

Carbomer, Triethanolamine, Emollients, Essence and purified water

Package Label - Principal Display Panel

60 mL NDC:75532-001-01

250 mL NDC:75532-001-02

500 mL NDC:75532-001-03

1000 mL NDC:75532-001-04

4000 mL NDC:75532-001-05